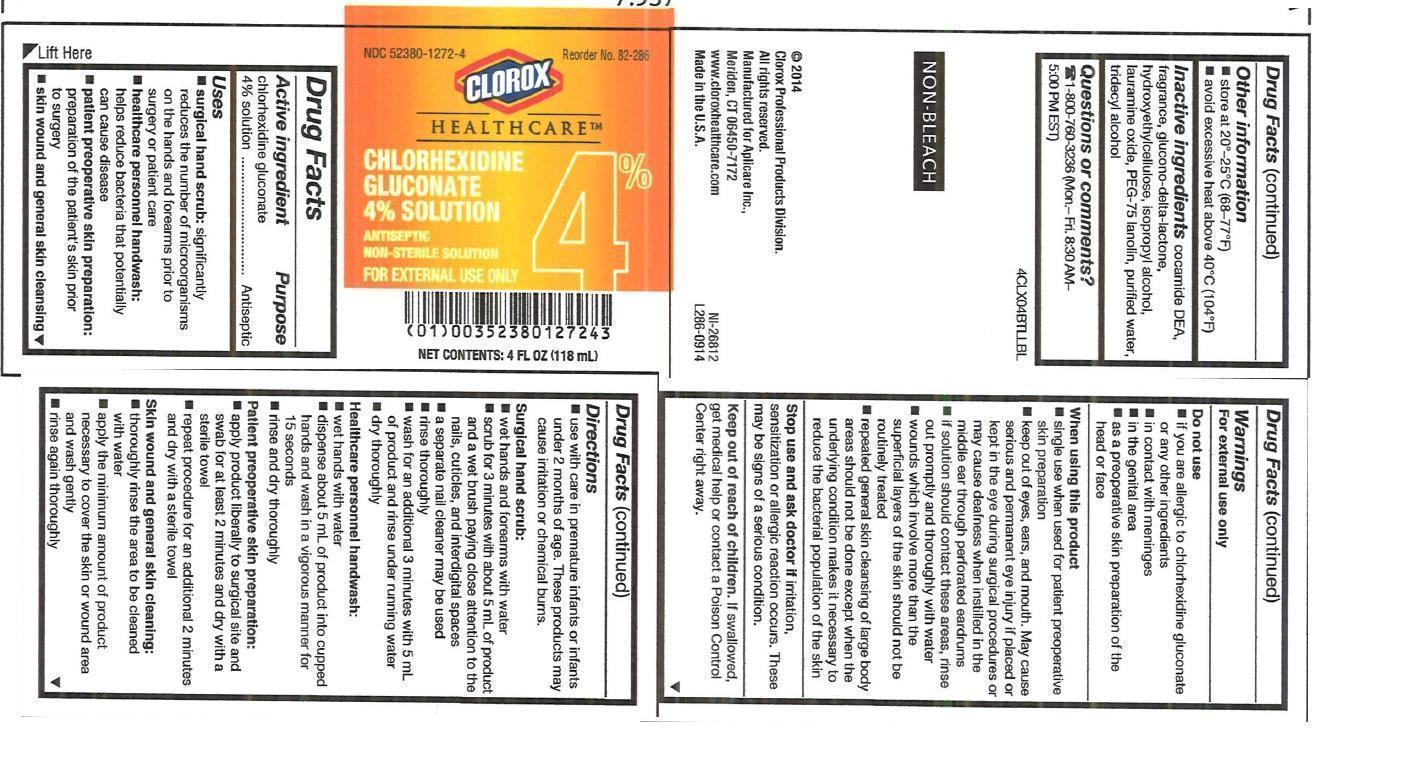 DRUG LABEL: 4% CHG Skin Cleansing Kit
NDC: 52380-7001 | Form: KIT | Route: Topical
Manufacturer: Aplicare, Inc.
Category: otc | Type: HUMAN OTC DRUG LABEL
Date: 20150820

ACTIVE INGREDIENTS: CHLORHEXIDINE GLUCONATE 4 g/100 mL
INACTIVE INGREDIENTS: COCO DIETHANOLAMIDE; GLUCONOLACTONE; HYDROXYETHYL CELLULOSE (140 CPS AT 5%); ISOPROPYL ALCOHOL; LAURAMINE OXIDE; WATER; TRIDECYL ALCOHOL; PEG-75 LANOLIN

Active ingredient

Chlorhexidine Gluconate 4% Solution

Purposes

surgical hand scrub

healthcare personnel handwash

patient preoperative skin preparation

skin wound and general skin cleansing

Uses

- surgical hand scrub: significantly reduces the number of microorganisms on the hands and forearms prior to surgery or patient care
- healthcare personnel handwash: handwash to help reduce bacteria that potentially can cause disease
- patient preoperative skin preparation: for the preparation of the patient's skin prior to surgery
- skin wound and general skin cleansing

Warnings

For external use only

Do not use:

- if you are allergic to chlorhexidine gluconate or any other ingredients
- in contact with meninges
- in the genital area
- as a preoperative skin preparation of the head or face

When using this product

- keep out of eyes, ears, and mouth. May cause serious and permanent eye injury if placed or kept in the eye during surgical procedures or may cause deafness when instilled in the middle ear through perforated ear drums.
- if solution should contact these areas, rinse out promptly and thoroughly with water
- wounds which involve more than the superficial layers layers of the skin should not be routinely treated
- repeated general skin cleansing of large body areas should not be done except when the underlying condition makes it necessary to reduce the bacterial population of the skin

Stop use and ask a doctor if irritation, sensitization or allergic reaction occurs. These may be signs of a serious condition.

Directions

Surgical hand scrub

- wet hands and forearms under running water for 30 seconds
- scrub for 3 minutes with about 5 mL of product with or without a wet brush, paying close attention to the nails, cuticles and interdigital spaces
- rinse thoroughly under running water for 30 seconds
- dry thoroughly

Healthcare personnel handwash

- wet hands with water
- dispense about 5 mL of product into cupped hands and wash in a vigorous manner for 15 seconds
- rinse and dry thoroughly

Patient preoperative skin preparation

- apply product liberally to surgical site and swab for at least 2 minutes
- dry with a sterile towel
- repeat procedure for an additional 2 minutes and dry with a sterile towel

Skin wound and general cleansing

- thoroughly rinse the area to be cleaned with water
- apply the minimum amount of product necessary to cover the skin or wound area and wash gently
- rinse again thoroughly

Other information

- store at 20-25 °C (68-77 °F)
- avoid excessive heat above 40 °C (104 °F)

Inactive ingredients

cocamide DEA, fragrance POFL 147, glucono-delta-lactone, hydroxyethylcellulose, isopropyl alcohol, lauramine oxide, PEG-75 lanolin, purified water, tridecyl alcohol

Questions or comments?

1-800-760-3236 (Mon. - Fri. - 8:30 AM - 5:00 PM EST)

PACKAGE LABEL

4% Chlorhexidine Gluconate, 128 oz